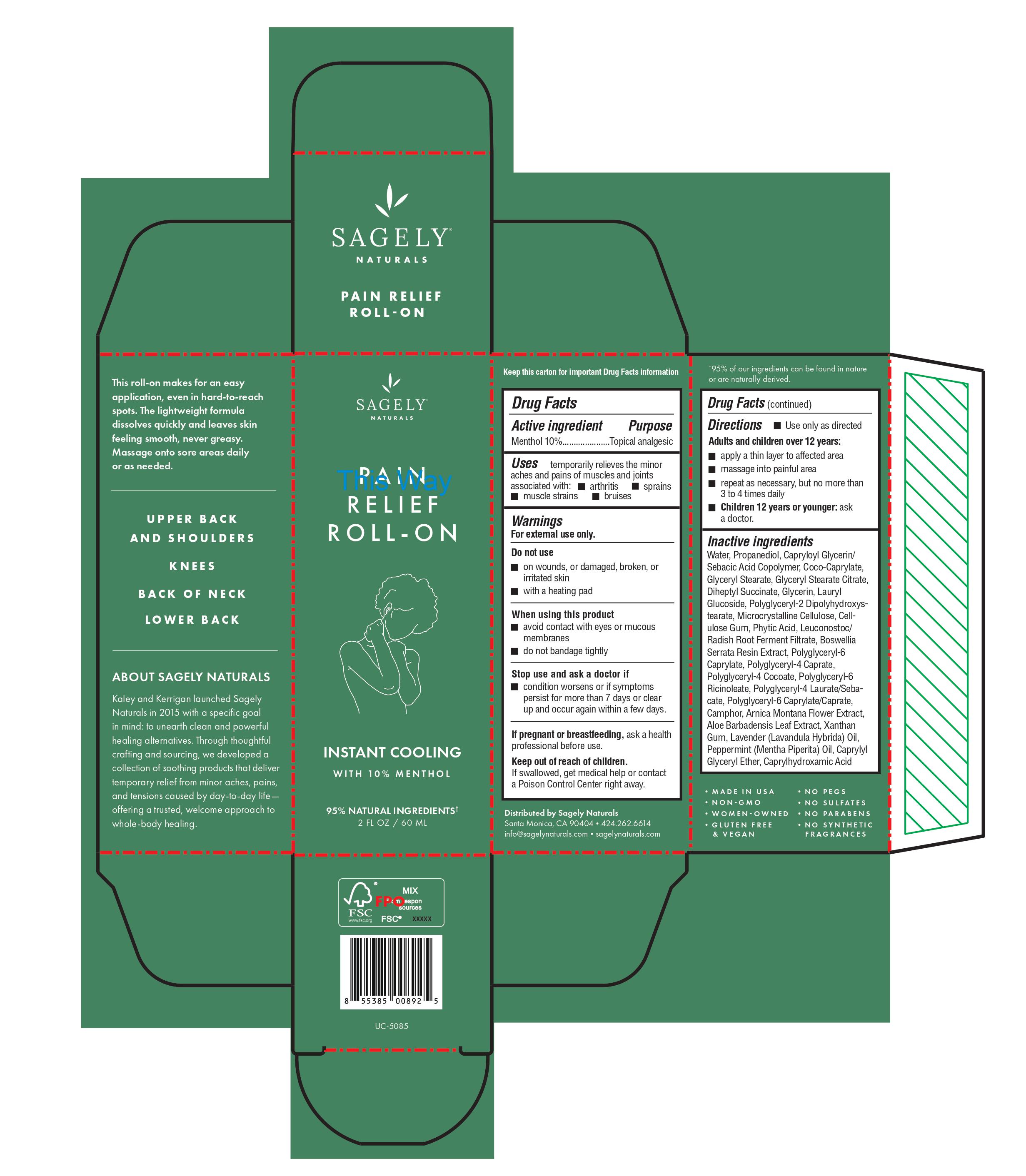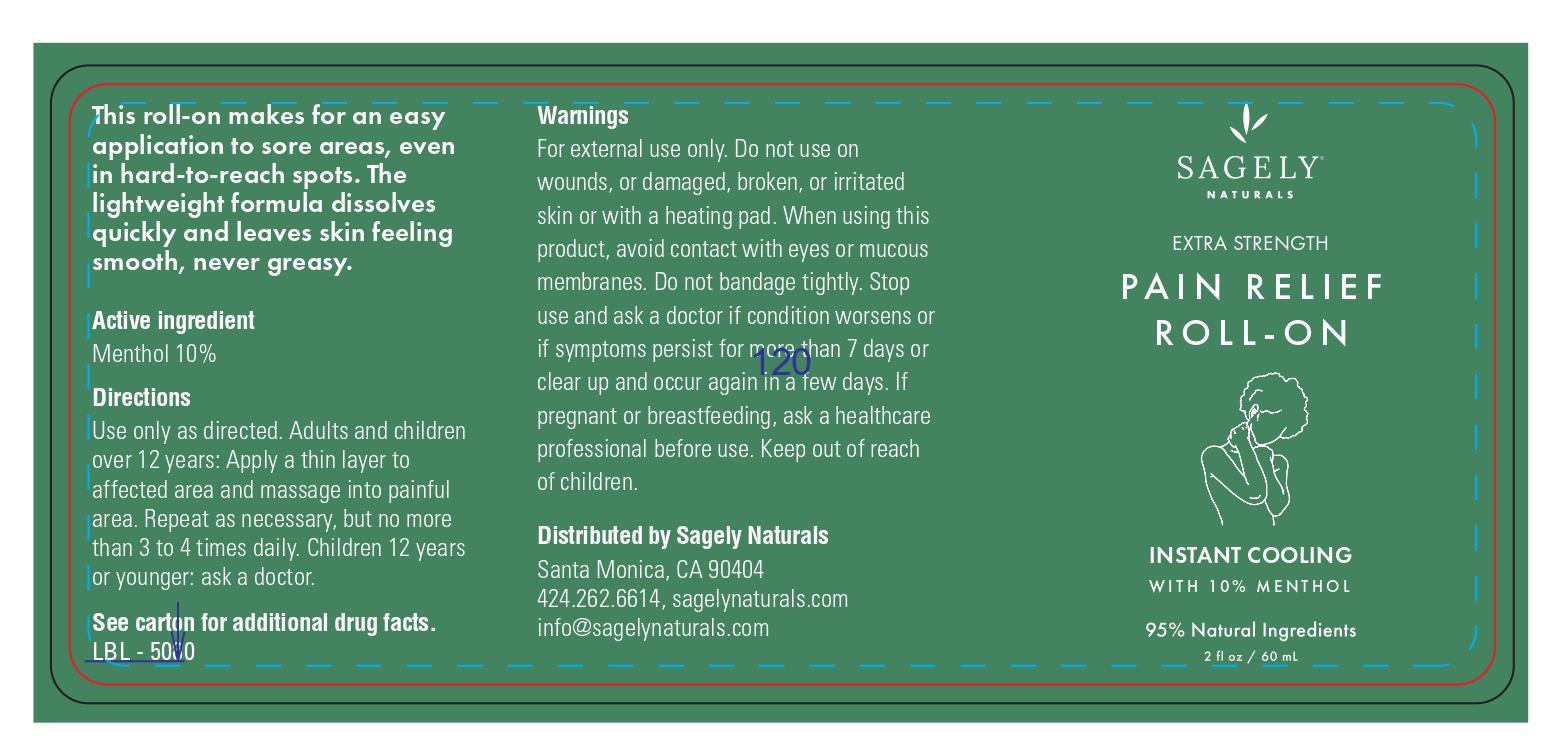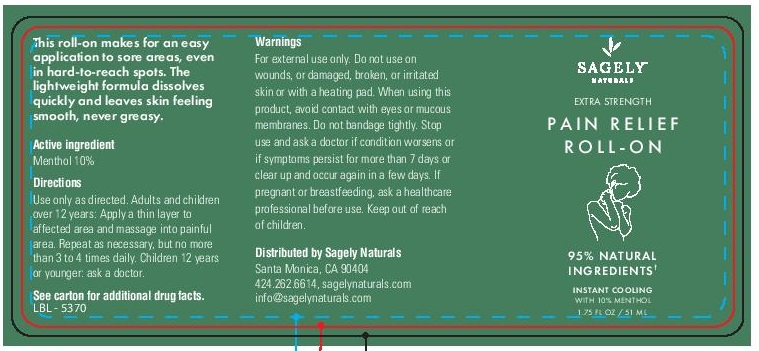 DRUG LABEL: Pain Relief Roll-On
NDC: 82075-420 | Form: LIQUID
Manufacturer: Sagely Enterprises Inc.
Category: otc | Type: HUMAN OTC DRUG LABEL
Date: 20211119

ACTIVE INGREDIENTS: MENTHOL 10 g/100 g
INACTIVE INGREDIENTS: LAVENDER OIL; PEPPERMINT OIL; LEUCONOSTOC/RADISH ROOT FERMENT FILTRATE; ARNICA MONTANA; GLYCERIN; LAURYL GLUCOSIDE; CARBOXYMETHYLCELLULOSE SODIUM, UNSPECIFIED; BOSWELLIA SERRATA RESIN OIL; PROPANEDIOL; POLYGLYCERYL-2 DIPOLYHYDROXYSTEARATE; MICROCRYSTALLINE CELLULOSE; POLYGLYCERYL-6 CAPRYLATE; POLYGLYCERYL-4 CAPRATE; POLYGLYCERYL-6 RICINOLEATE; CAMPHOR (NATURAL); ALOE VERA LEAF; XANTHAN GUM; WATER; CAPRYLOYL GLYCERIN/SEBACIC ACID COPOLYMER (2000 MPA.S); COCO-CAPRYLATE; GLYCERYL STEARATE CITRATE; GLYCERYL MONOSTEARATE; DIHEPTYL SUCCINATE; FYTIC ACID; CAPRYLYL GLYCERYL ETHER; CAPRYLHYDROXAMIC ACID

Pain Relief Roll-On

Active ingredient

Menthol 10%

Purpose

Menthol 10%.................Topical analgesic

Uses

temporarily relieves the minor aches and pains of muscles and joints associated with:

- arthritis
- sprains
- muscle strains
- bruises

Warnings

For external use only.

Do not use

- on wounds, or damaged, broken, or irritated skin
- with a heating pad

When using this product

- avoid contact with eyes or mucous membranes
- do not bandage tightly

Stop use and ask a doctor if

- condition worsens or if symptoms persist for more than 7 days or clear up and occur again within a few days.

PREGNANCY OR BREAST FEEDING

If pregnant or breastfeeding, ask a health professional before use.

Keep out of reach of children. If swallowed, get medical help or contact a Poison Control Center right away.

Directions

- Use only as directed

Adults and children over 12 years:

- apply a thin layer to affected area
- massage into painful area
- repeat as necessary, but no more than 3 to 4 times daily
- Children 12 years or younger: ask a doctor.

Inactive ingredients

Water, Propanediol, Capryloyl Glycerin/Sebacic Acid Copolymer, Coco-Caprylate, Glyceryl Stearate, Glyceryl Stearate Citrate, Diheptyl Succinate, Glycerin, Lauryl Glucoside, Polyglyceryl-2 Dipolyhydroxystearate, Microcrystalline Cellulose, Cellulose Gum, Phytic Acid, Leuconostoc/Radish Root Ferment Filtrate, Boswellia Serrata Resin Extract, Polyglyceryl-6 Caprylate, Polyglyceryl-4 Caprate, Polyglyceryl-4 Cocoate, Polyglyceryl-6 Ricinoleate, Polyglyceryl-4 Laurate/Sebacate, Polyglyceryl-6 Caprylate/Caprate, Camphor, Arnica Montana Flower Extract, Aloe Barbadensis Leaf Extract, Xanthan Gum, Lavender (Lavandula Hybrida) Oil, Peppermint (Mentha Piperita) Oil, Caprylyl Glyceryl Ether, Caprylhydroxamic Acid

PACKAGE LABEL

Sagely Naturals

Pain Relief Roll-On

Instant Cooling

With 10% Menthol

95% Natural Ingredients

2 FL OZ / 60 ML